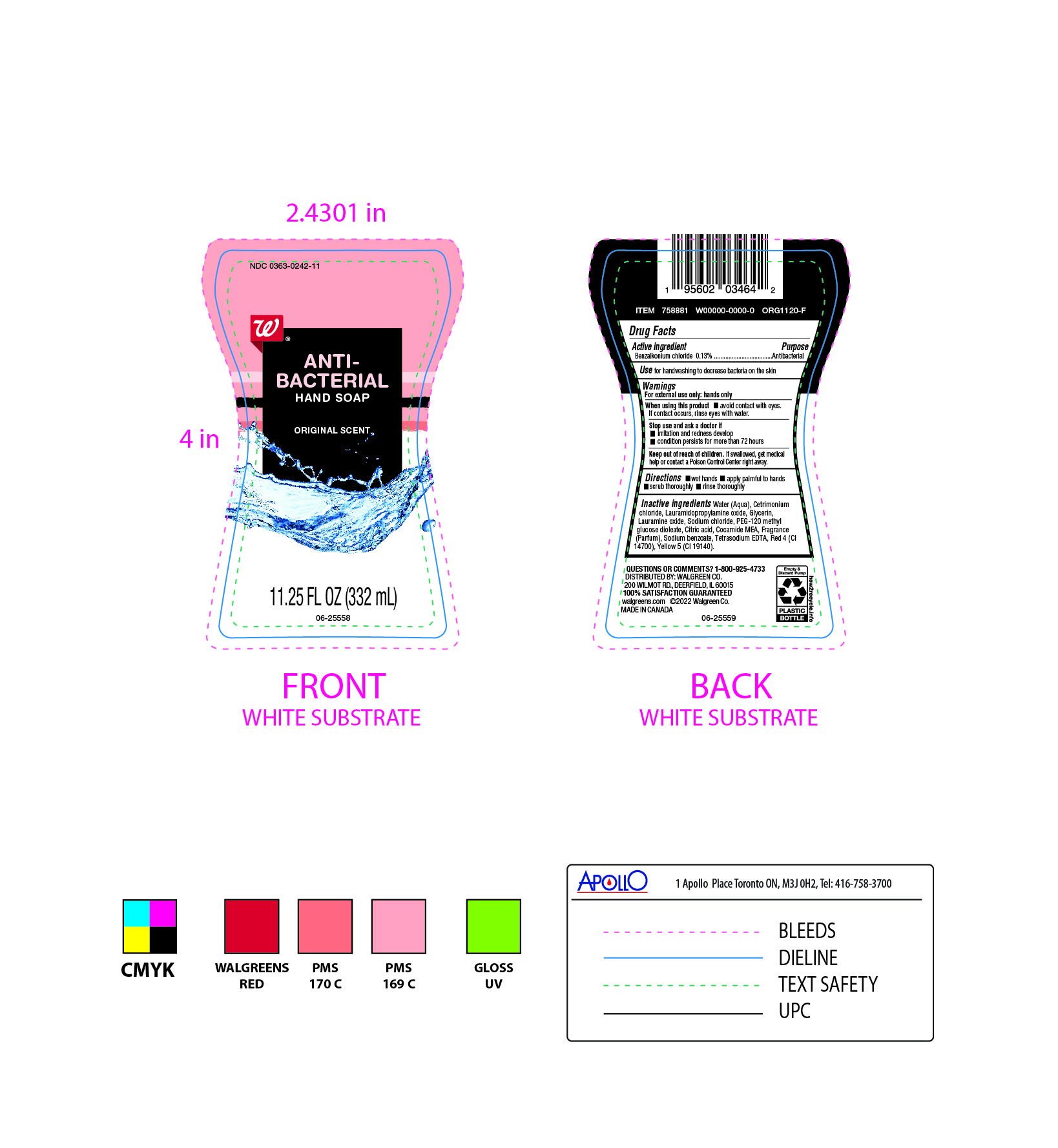 DRUG LABEL: Walgreen
NDC: 0363-0242 | Form: SOAP
Manufacturer: Walgreen
Category: otc | Type: HUMAN OTC DRUG LABEL
Date: 20241008

ACTIVE INGREDIENTS: BENZALKONIUM CHLORIDE 130 mg/100 mL
INACTIVE INGREDIENTS: GLYCERIN; PEG-120 METHYL GLUCOSE DIOLEATE; COCO MONOETHANOLAMIDE; FD&C RED NO. 4; LAURAMIDOPROPYLAMINE OXIDE; FRAGRANCE CLEAN ORC0600327; WATER; SODIUM CHLORIDE; CITRIC ACID MONOHYDRATE; CETRIMONIUM CHLORIDE; LAURAMINE OXIDE; SODIUM BENZOATE; FD&C YELLOW NO. 5; EDETATE SODIUM

Walgreens Handsoap 0363-0242-11

DOSAGE AND ADMINISTRATION

-wet hands

-apply palmful to hands

-scrub thoroughly

-rinse thoroughly